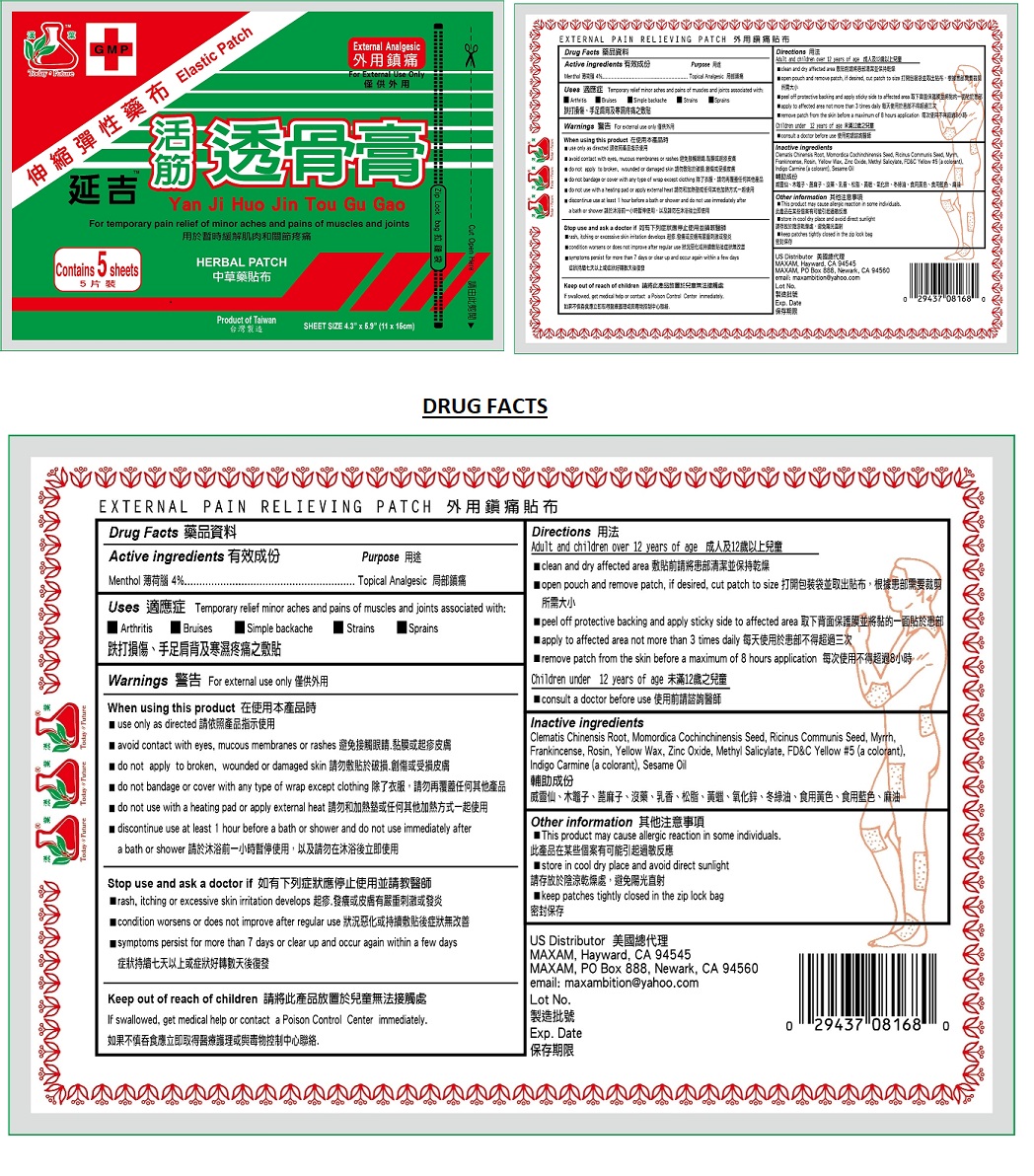 DRUG LABEL: Yan Ji Huo Jin Tou Gu Gao
NDC: 72183-769 | Form: PATCH
Manufacturer: MAXAM
Category: otc | Type: HUMAN OTC DRUG LABEL
Date: 20180122

ACTIVE INGREDIENTS: MENTHOL, UNSPECIFIED FORM 4 g/100 g
INACTIVE INGREDIENTS: CLEMATIS CHINENSIS ROOT; MOMORDICA COCHINCHINENSIS SEED; RICINUS COMMUNIS SEED; MYRRH; FRANKINCENSE; ROSIN; YELLOW WAX; ZINC OXIDE; METHYL SALICYLATE; FD&C YELLOW NO. 5; INDIGOTINDISULFONATE SODIUM; SESAME OIL

Yan Ji Huo Jin Tou Gu Gao

Active ingredients

Menthol 4%

Purpose

Topical Analgesic

Uses

Temporary relief minor aches and pains of muscles and joints associated with:

• Arthritis • Bruises • Simple backache • Strains • Sprains

Warnings:

For external use only

When using this product

• use only as directed

• avoid contact with eyes, mucous membranes or rashes

• do not apply to broken, wounded or damaged skin

• do not bandage or cover with any type of wrap except clothing

• do not use with a heating pad or apply external heat

• discontinue use at least 1 hour before a bath or shower and do not use immediately after a bath or shower

Stop use and ask a doctor if

• rash, itching or excessive skin irritation develops

• condition worsens or does not improve after regular use

• symptoms persist for more than 7 days or clear up and occur again within a few days

Keep out of reach of children

If swallowed, get medical help or contact a Poison Control Center immediately

Directions:

Adult and children over 12 years of age:

• clean and dry affected area

• open pouch and remove patch, if desired, cut patch to size

• peel off protective backing and apply sticky side to affected area

• apply to affected area not more than 3 times daily

• remove patch from the skin before a maximum 8 hours application.

Children under 12 years of age

• consult a doctor before use

Inactive ingredients:

Clematis Chinensis Root, Momordica Cochinchinensis Seed, Ricinus Communis Seed, Myrrh, Frankincense, Rosin, Yellow Wax, Zinc Oxide, Methyl Salicylate, FD&C Yellow #5 (a colorant), Indigo Carmine (a colorant), Sesame Oil

Other information:

• This product may cause allergic reaction in some individuals.

• store in cool dry place and avoid direct sunlight

• keep patches tightly closed in the zip lock bag

EXTERNAL PAIN RELIEVING PATCH

Elastic Patch

HERBAL PATCH

Product of Taiwan

US Distributor:

MAXAM, Hayward, CA 94545

MAXAM, PO Box 888, Newark, CA 94560

email:maxambition@yahoo.com